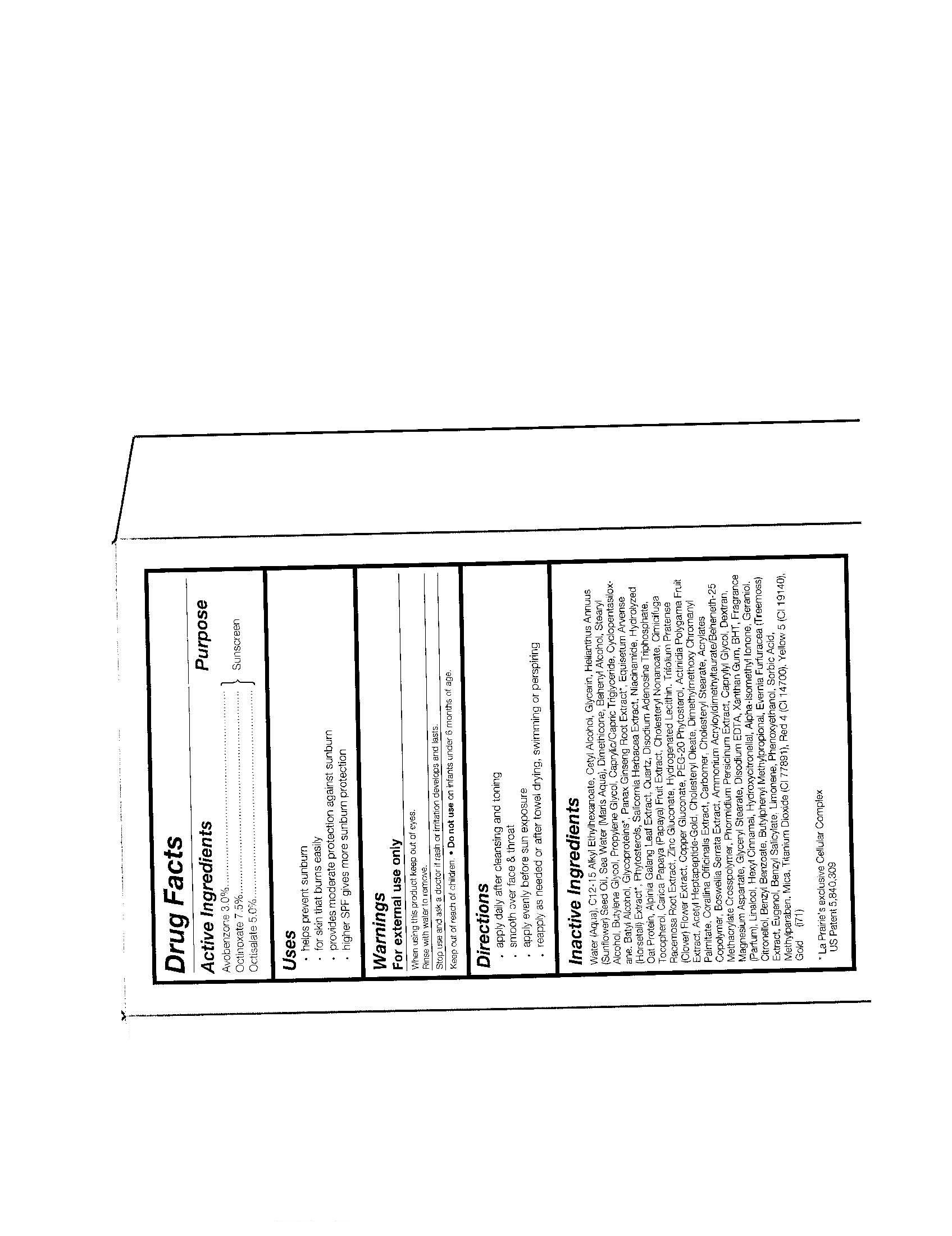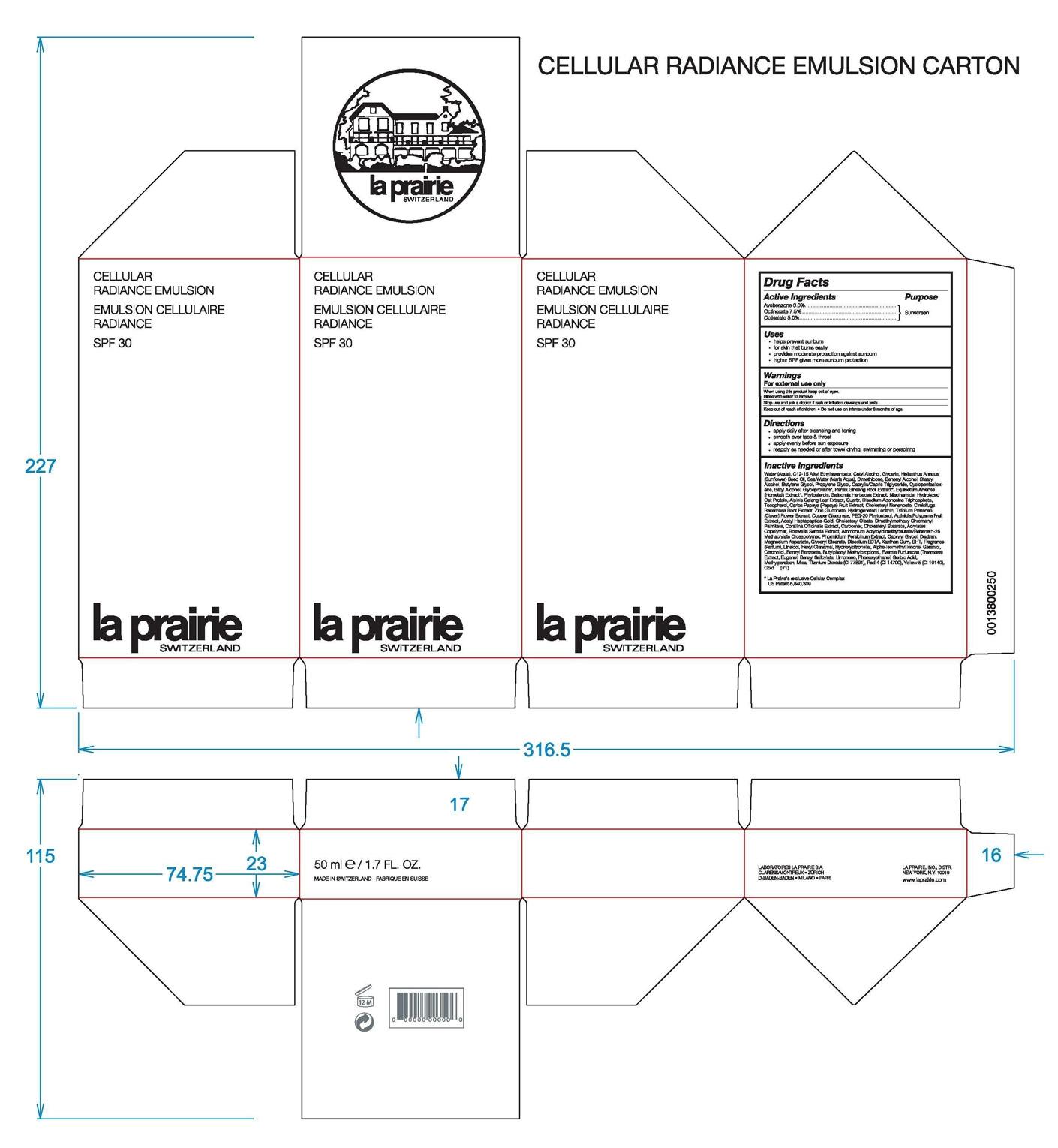 DRUG LABEL: La Prairie Switzerland
NDC: 68807-301 | Form: CREAM
Manufacturer: Temmentec Ag
Category: prescription | Type: HUMAN PRESCRIPTION DRUG LABEL
Date: 20100525

ACTIVE INGREDIENTS: AVOBENZONE 3.0 kg/100 kg; OCTINOXATE 7.5 kg/100 kg; OCTISALATE 5.0 kg/100 kg

Cellular Radiance Emulsion

Active Ingredients Purpose

Avobenzone 3.0% Sunscreen

Octinoxate 7.5% Sunscreen

Octisalate 5.0% Sunscreen

Warnings

-for external use only

-when using this product keep out of eyes

-rinse with water to remove

-stop use and ask a doctor if rash or irritation develops and lasts

-keep out of reach of children

-do not use on infants under 6 months of age

Uses

-helps prevent sunburn

-for skin that burns easily

-provides moderate protection against sunburn

-higher SPF gives more sunburn protection

Directions

-for external use only

-when using this product keep out of eyes

-rinse with water to remove

-stop use and ask doctor if rash or irritation develops and lasts

-keep out of reach of children

-do not use on infants under 6 months of age

INACTIVE INGREDIENT

Inactive Ingredients: Water (Aqua), C12-15 Alkyl Ethylhexanoate, Cetyl Alcohol, Glycerin, Helianthus Annuus (Sunflower) Seed Oil, Sea Water (Maris Aqua), Dimethicone, Behenyl Alcohol, Stearyl Alcohol, Butylene Glycol, Propylene Glycol, Caprylic/Capric Triglyceride, Cyclopentasiloxane, Batyl Alcohol, Glycoproteins, Panax Ginseng Root Extract, Equisetum Arvense (Horsetail) Extract, Phytosterols, Silicornia Herbacea Extract, Niacinamide, Hydrolyzed Oat Protein, Alpinia Galang Leaf Extract, Quartz, Disodium Adenosine Triphosphate, Tocopherol, Carica Papaya (Papaya) Fruit Extract, Cholesteryl Nonanoate, Cimicifuga Racemosa Root Extract, Copper Gluconate, PEG-20 Phytosterol, Actinidia Polygama Fruit Extract, Acetyl Heptapeptide-Gold, Cholesteryl Oleate, Dimethylmethoxy Chromanyl Palmitate, Corallina Officinalis Extract, Carbomer, Cholsteryl Stearate, Acrylates Copolymer, Boswellia Serrata Extract, Ammonium Acryloyldimethltaurate/Beheneth-25 Methacrylate Crosspolymer, Phormidium Persicinum Extract, Caprylyl Glycol, Dextran, Magnesium Asparate Glyceryl Stearate, Disodium EDTA, Xanthan Gum, BHT, Fragrance (Parfum), Linalool, Hexyl Cinnamal, Hydroxycitronellal, Alpha-Isomethyl Ionone, Geraniol, Citronellol, Benzyl Benzoate, Butylphenyl Methylpropional, Evernia Furfuracea (Treemoss) Extract, Eugenol, Benzyl Salicylate, Limonene, Phenoxyethanol, Sorbia Acid, Methylparaben, Mica, Titanium Dioxide (CI 77891), Red (CI 14700), Yellow 5 (CI 19140), Gold

PACKAGE LABEL

Cellular Radiance Emulsion

SPF 30

50 ml / 1.7 Fl. Oz.